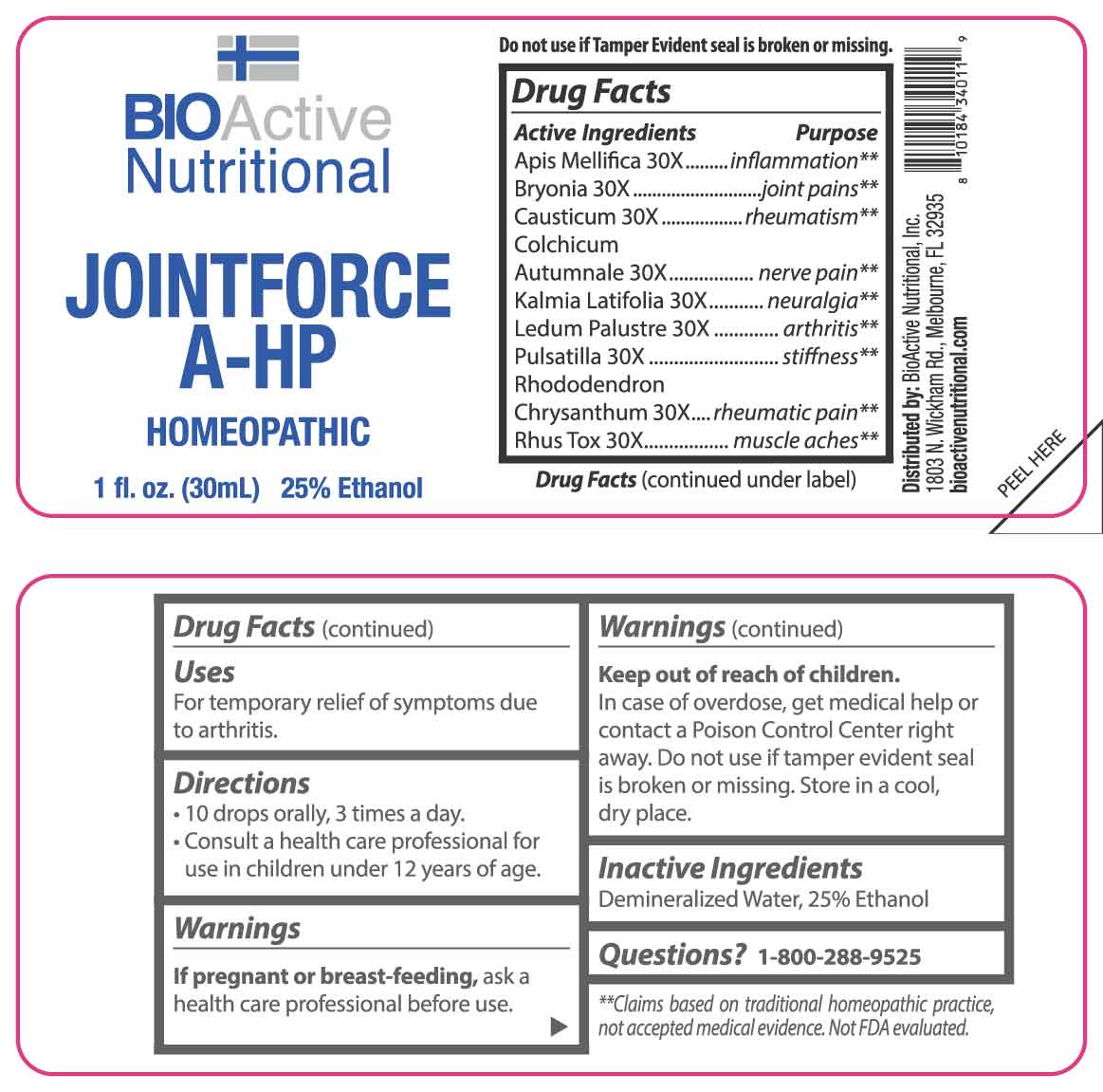 DRUG LABEL: Jointforce A-HP
NDC: 43857-0581 | Form: LIQUID
Manufacturer: BioActive Nutritional, Inc.
Category: homeopathic | Type: HUMAN OTC DRUG LABEL
Date: 20250403

ACTIVE INGREDIENTS: APIS MELLIFERA 30 [hp_X]/1 mL; BRYONIA ALBA ROOT 30 [hp_X]/1 mL; CAUSTICUM 30 [hp_X]/1 mL; COLCHICUM AUTUMNALE BULB 30 [hp_X]/1 mL; KALMIA LATIFOLIA LEAF 30 [hp_X]/1 mL; RHODODENDRON TOMENTOSUM LEAFY TWIG 30 [hp_X]/1 mL; PULSATILLA VULGARIS WHOLE 30 [hp_X]/1 mL; RHODODENDRON AUREUM LEAF 30 [hp_X]/1 mL; TOXICODENDRON PUBESCENS LEAF 30 [hp_X]/1 mL
INACTIVE INGREDIENTS: WATER; ALCOHOL

DRUG FACTS:

ACTIVE INGREDIENTS:

Apis Mellifica 30X, Bryonia 30X, Causticum 30X, Colchicum Autumnale 30X, Kalmia Latifolia 30X, Ledum Palustre 30X, Pulsatilla 30X, Rhododendron Chrysanthum 30X, Rhus Tox 30X.

PURPOSE:

Apis Mellifica- inflammation,** Bryonia – joint pains,** Causticum - rheumatism,** Colchicum Autumnale – nerve pain,** Kalmia Latifolia - neuralgia,** Ledum Palustre - arthritis,** Pulsatilla - stiffness,** Rhododendron Chrysanthum – rheumatic pain,** Rhus Tox – muscle aches**
**Claims based on traditional homeopathic practice, not accepted medical evidence. Not FDA Evaluated.

USES:

For temporary relief of symptoms due to arthritis.

WARNINGS:

If pregnant or breast-feeding, ask a health care professional before use.

Keep out of reach of children. In case of overdose, get medical help or contact a Poison Control Center right away.

Do not use if tamper evident seal is broken or missing.

Store in a cool, dry place.

KEEP OUT OF REACH OF CHILDREN:

In case of overdose, get medical help or contact a Poison Control Center right away.

DIRECTIONS:

• 10 drops orally, 3 times a day.

• Consult a health care professional for use in children under 12 years of age.

INACTIVE INGREDIENTS:

Demineralized Water, 25% Ethanol

QUESTIONS:

Distributed by:
BioActive Nutritional, Inc.
1803 N. Wickham Rd.
Melbourne, FL 32935
bioactivenutritional.com

1-800-288-9525

PACKAGE LABEL DISPLAY:

BIOActive Nutritional

JOINTFORCE A-HP

HOMEOPATHIC

1 FL OZ (30 ml)